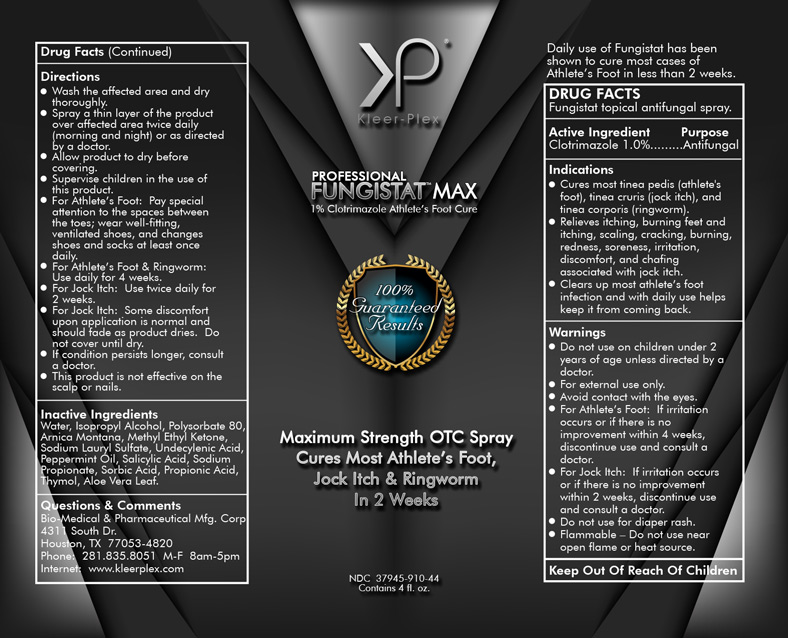 DRUG LABEL: Fungistat Max
NDC: 37945-910 | Form: LIQUID
Manufacturer: Bio-Medical & Pharmaceutical Manufacturing Corporation
Category: otc | Type: HUMAN OTC DRUG LABEL
Date: 20160408

ACTIVE INGREDIENTS: CLOTRIMAZOLE 10 mg/1 mL
INACTIVE INGREDIENTS: ALOE VERA LEAF; PEPPERMINT OIL; SODIUM PROPIONATE; SORBIC ACID; PROPIONIC ACID; WATER; ARNICA MONTANA; SODIUM LAURYL SULFATE; SALICYLIC ACID; THYMOL; ISOPROPYL ALCOHOL; POLYSORBATE 80; METHYL ETHYL KETONE; UNDECYLENIC ACID

Drug Facts

Fungistat topical antifungal spray.

Active Ingredient

Clotrimazole 1.0%

Purpose

Antifungal

Indications

- Cures most tinea pedis (athlete's foot), tinea cruris (jock itch), and tinea corporis (ringworm).
- Relieves itching, burning feet and itching, scaling, cracking, burning, redness, soreness, irritation, discomfort, and chafing associated with jock itch.
- Clears up most athlete’s foot infection and with daily use helps keep it from coming back.

Warnings

- Do not use on children under 2 years of age unless directed by a doctor.
- For external use only.
- Avoid contact with the eyes.
- For Athlete’s Foot: If irritation occurs or if there is no improvement within 4 weeks, discontinue use and consult a doctor.
- For Jock Itch: If irritation occurs or if there is no improvement within 2 weeks, discontinue use and consult a doctor.
- Do not use for diaper rash.
- Flammable – Do not use near open flame or heat source.

Directions

- Wash the affected area and dry thoroughly.
- Spray a thin layer of the product over affected area twice daily (morning and night) or as directed by a doctor.
- Allow product to dry before covering.
- Supervise children in the use of this product.
- For Athlete’s Foot: Pay special attention to the spaces between the toes; wear well-fitting, ventilated shoes, and changes shoes and socks at least once daily.
- For Athlete’s Foot & Ringworm: Use daily for 4 weeks.
- For Jock Itch: Use daily for 2 weeks.
- For Jock Itch: Some discomfort upon application is normal and should fade as product dries. Do not cover until dry.
- If condition persists longer, consult a doctor.
- This product is not effective on the scalp or nails.

Inactive Ingredients

Water, Isopropyl Alcohol, Polysorbate 80, Arnica Montana, Methyl Ethyl Ketone, Sodium Lauryl Sulfate, Undecylenic Acid, Peppermint Oil, Salicylic Acid, Sodium Propionate, Sorbic Acid, Propionic Acid, Thymol, Aloe Vera Leaf.

Questions & Comments

Bio-Medical & Pharmaceutical Manufacturing Corporation

4311 South Dr., Houston, TX 77053-4820

Phone: 281.835.8051 M-F 8am-5pm

Internet: www.kleerplex.com

PACKAGE LABEL

Professional Fungistat Max

1% Clotrimazole Athlete's Foot Care

Maximum Strength OTC Spray

Cures Most Athlete's Foot, Jock Itch & Ringworm In 2 Weeks

NDC 37945-910-44

Contains 4 fl. oz